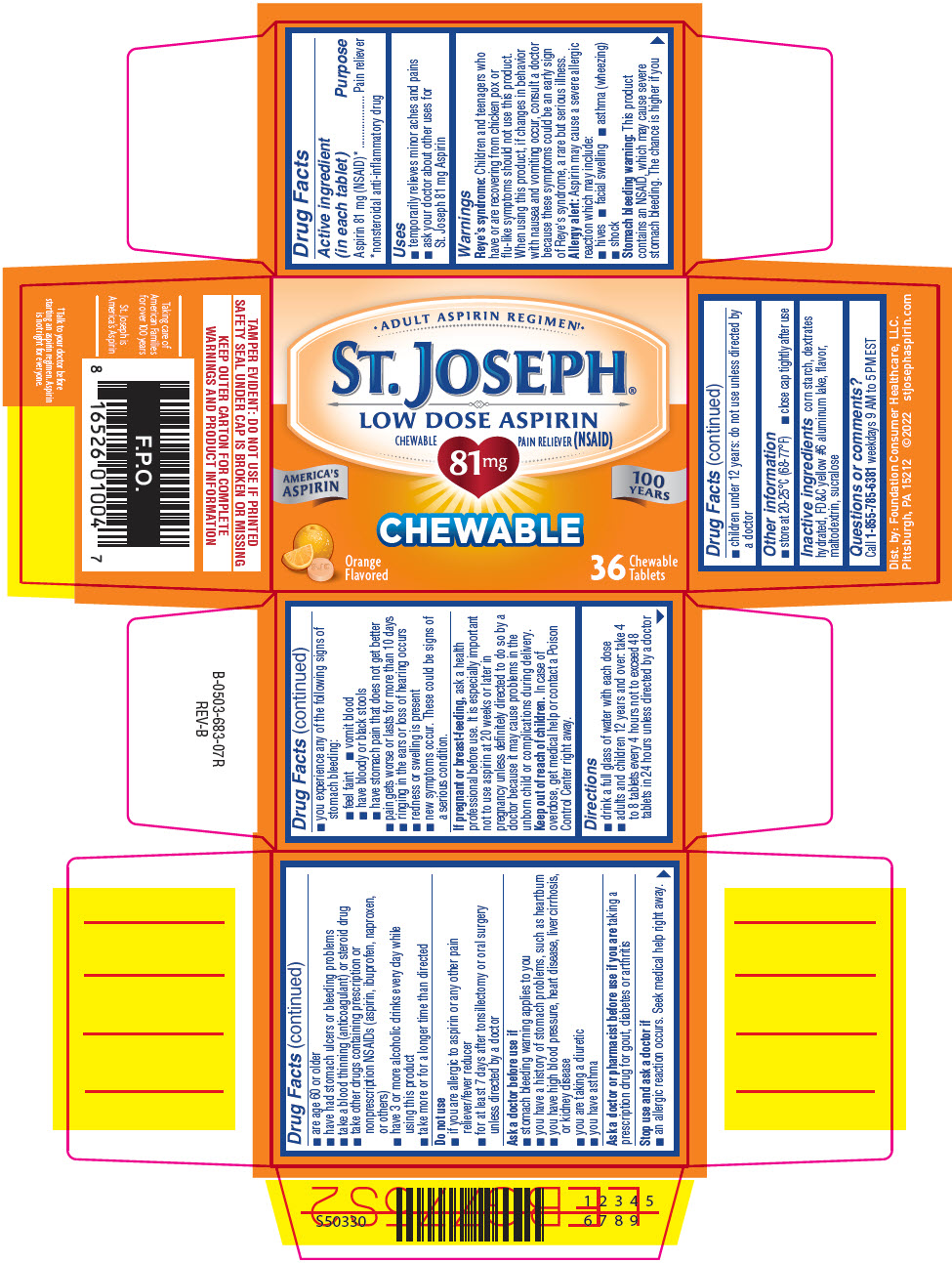 DRUG LABEL: St. Joseph Chewable Low Dose Aspirin
NDC: 69536-281 | Form: TABLET, CHEWABLE
Manufacturer: Foundation Consumer Healthcare LLC
Category: otc | Type: HUMAN OTC DRUG LABEL
Date: 20241202

ACTIVE INGREDIENTS: ASPIRIN 81 mg/1 1
INACTIVE INGREDIENTS: STARCH, CORN; DEXTRATES; FD&C YELLOW NO. 6; MALTODEXTRIN; SUCRALOSE

St. Joseph®Chewable Low Dose Aspirin

Drug Facts

Active ingredient (in each tablet)

Aspirin 81 mg (NSAID) [nonsteroidal anti-inflammatory drug]

Purpose

Pain reliever

Uses

- temporarily relieves minor aches and pains
- ask your doctor about other uses for St. Joseph Safety Coated 81 mg Aspirin

Warnings

Reye's syndrome

Children and teenagers who have or are recovering from chicken pox or flu-like symptoms should not use this product. When using this product, if changes in behavior with nausea and vomiting occur, consult a doctor because these symptoms could be an early sign of Reye's syndrome, a rare but serious illness.

Allergy alert

Aspirin may cause a severe allergic reaction which may include:

- hives
- facial swelling
- asthma (wheezing)
- shock

Stomach bleeding warning

This product contains an NSAID, which may cause severe stomach bleeding. The chance is higher if you

- are age 60 or older
- have had stomach ulcers or bleeding problems
- take a blood thinning (anticoagulant) or steroid drug
- take other drugs containing prescription or nonprescription NSAIDs (aspirin, ibuprofen, naproxen, or others)
- have 3 or more alcoholic drinks every day while using this product
- take more or for a longer time than directed

Do not use

- if you are allergic to aspirin or any other pain reliever/fever reducer
- for at least 7 days after tonsillectomy or oral surgery unless directed by a doctor

Ask a doctor before use if

- stomach bleeding warning applies to you
- you have a history of stomach problems, such as heartburn
- you have high blood pressure, heart disease, liver cirrhosis, or kidney disease
- you are taking a diuretic
- you have asthma

Ask a doctor or pharmacist before use if you aretaking a prescription drug for gout, diabetes or arthritis

Stop use and ask a doctor if

- an allergic reaction occurs. Seek medical help right away.
- you experience any of the following signs of stomach bleeding:
  - feel faint
  - vomit blood
  - have bloody or black stools
  - have stomach pain that does not get better
- pain gets worse or lasts for more than 10 days
- ringing in the ears or loss of hearing occurs
- redness or swelling is present
- new symptoms occur. These could be signs of a serious condition.

PREGNANCY OR BREAST FEEDING

If pregnant or breast-feeding,ask a health professional before use. It is especially important not to use aspirin 20 weeks or later in pregnancy unless definitely directed to do so by a doctor because it may cause problems in the unborn child or complications during delivery.

Keep out of reach of children.In case of overdose, get medical help or contact a Poison Control Center right away.

Directions

- drink a full glass of water with each dose
- adults and children 12 years and over: take 4 to 8 tablets every 4 hours not to exceed 48 tablets in 24 hours unless directed by a doctor
- children under 12 years: do not use unless directed by a doctor

Other information

- store at 20-25°C (68-77°F)
- close cap tightly after use

Inactive ingredients

corn starch, dextrates hydrated, FD&C yellow #6 aluminum lake, flavor, maltodextrin, sucralose

Questions or comments?

Call 1-855-785-6381weekdays 9 AM to 5 PM EST

Dist. by: Foundation Consumer Healthcare, LLC.
Pittsburgh, PA 15205

PRINCIPAL DISPLAY PANEL - 36 Tablet Bottle Box

• ADULT ASPIRIN REGIMEN†•

ST. JOSEPH®
LOW DOSE ASPIRIN
CHEWABLE PAIN RELIEVER (NSAID)

81 mg

AMERICA'S
ASPIRIN

100
YEARS

CHEWABLE

Orange
Flavored

36
Chewable
Tablets